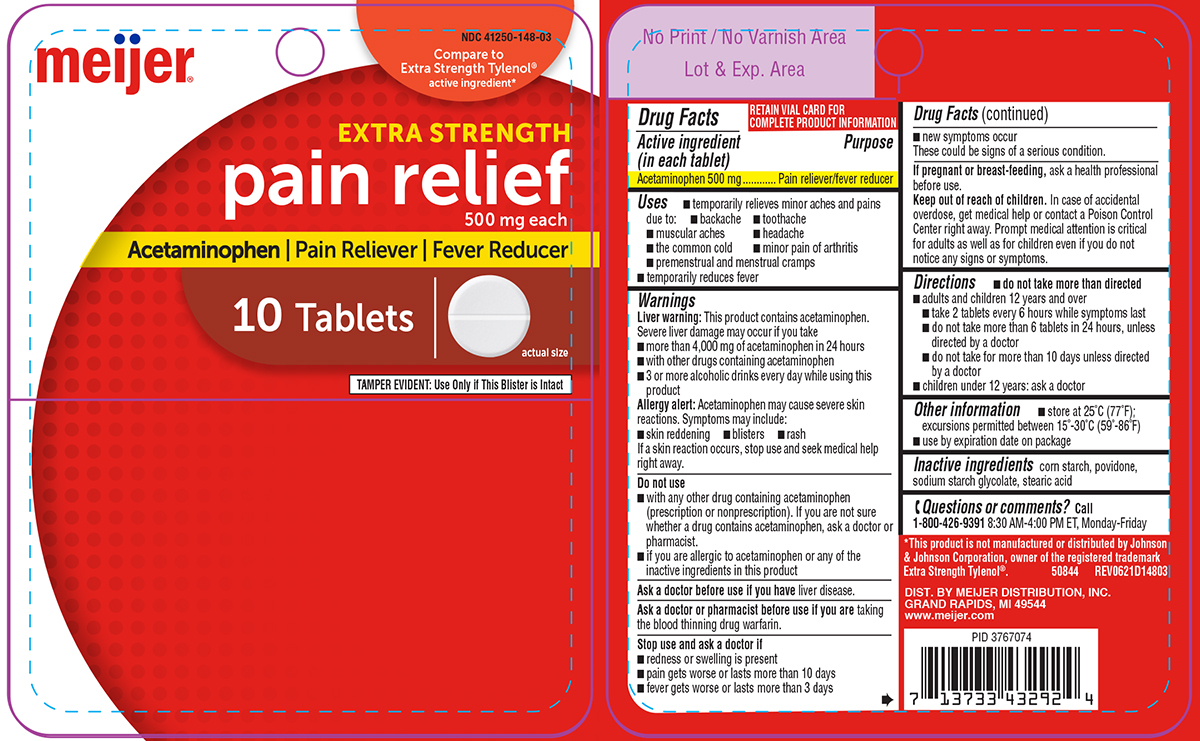 DRUG LABEL: Pain Relief
NDC: 41250-148 | Form: TABLET
Manufacturer: Meijer Distribution Inc
Category: otc | Type: HUMAN OTC DRUG LABEL
Date: 20260204

ACTIVE INGREDIENTS: ACETAMINOPHEN 500 mg/1 1
INACTIVE INGREDIENTS: STARCH, CORN; POVIDONE, UNSPECIFIED; SODIUM STARCH GLYCOLATE TYPE A POTATO; STEARIC ACID

Meijer 44-148 Delisted

Active ingredient (in each tablet)

Acetaminophen 500 mg

Purpose

Pain reliever/fever reducer

Uses

- temporarily relieves minor aches and pains due to:
  - backache
  - toothache
  - muscular aches
  - headache
  - the common cold
  - minor pain of arthritis
  - premenstrual and menstrual cramps
- temporarily reduces fever

Warnings

Liver warning: This product contains acetaminophen. Severe liver damage may occur if you take

- more than 4,000 mg of acetaminophen in 24 hours
- with other drugs containing acetaminophen
- 3 or more alcoholic drinks every day while using this product

Allergy alert: Acetaminophen may cause severe skin reactions. Symptoms may include:

- skin reddening
- blisters
- rash

If a skin reaction occurs, stop use and seek medical help right away.

Do not use

- with any other drug containing acetaminophen (prescription or nonprescription). If you are not sure whether a drug contains acetaminophen, ask a doctor or pharmacist.
- if you are allergic to acetaminophen or any of the inactive ingredients in this product

Ask a doctor before use if you have

liver disease.

Ask a doctor or pharmacist before use if you are

taking the blood thinning drug warfarin.

Stop use and ask a doctor if

- redness or swelling is present
- pain gets worse or lasts more than 10 days
- fever gets worse or lasts more than 3 days
- new symptoms occur

These could be signs of a serious condition.

If pregnant or breast-feeding,

ask a health professional before use.

Keep out of reach of children.

In case of accidental overdose, get medical help or contact a Poison Control Center right away. Prompt medical attention is critical for adults as well as for children even if you do not notice any signs or symptoms.

Directions

- do not take more than directed
- adults and children 12 years and over
  - take 2 tablets every 6 hours while symptoms last
  - do not take more than 6 tablets in 24 hours, unless directed by a doctor
  - do not take for more than 10 days unless directed by a doctor
- children under 12 years: ask a doctor

Other information

- store at 25ºC (77ºF); excursions permitted between 15º-30ºC (59º-86ºF)
- use by expiration date on package

Inactive ingredients

corn starch, povidone, sodium starch glycolate, stearic acid

Questions or comments?

Call 1-800-426-9391 8:30 AM-4:00 PM ET, Monday- Friday

Principal Display Panel

NDC 41250-148-03

meijer®

Compare to
Extra Strength Tylenol®
active ingredient*

EXTRA STRENGTH
pain relief
500 mg each
Acetaminophen | Pain Reliever | Fever Reducer

10 Tablets

actual size

TAMPER EVIDENT: Use Only if This Blister is Intact

*This product is not manufactured or distributed by Johnson
& Johnson Corporation, owner of the registered trademark
Extra Strength Tylenol®. 50844 REV0621D14803

DIST. BY MEIJER DISTRIBUTION, INC.
GRAND RAPIDS, MI 49544
www.meijer.com

Meijer 44-148